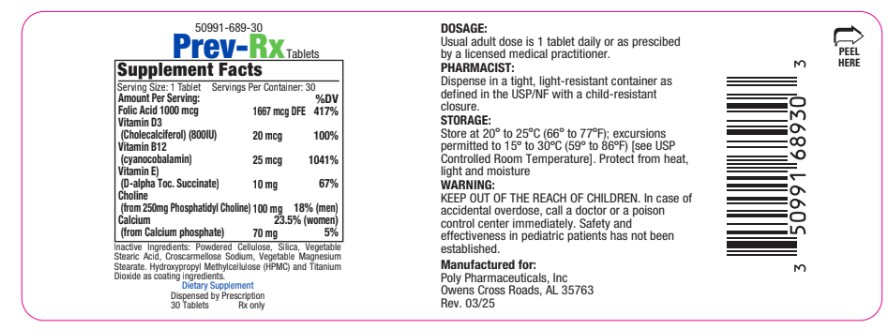 DRUG LABEL: Prev-Rx
NDC: 50991-689 | Form: TABLET
Manufacturer: Poly Pharmaceuticals, Inc
Category: other | Type: Dietary Supplement
Date: 20250513

ACTIVE INGREDIENTS: FOLIC ACID 1000 ug/1 1; CHOLECALCIFEROL 20 ug/1 1; CYANOCOBALAMIN 25 ug/1 1; .ALPHA.-TOCOPHEROL SUCCINATE, D- 10 mg/1 1; CHOLINE 100 mg/1 1; CALCIUM 70 mg/1 1
INACTIVE INGREDIENTS: POWDERED CELLULOSE; SILICA; STEARIC ACID; CROSCARMELLOSE SODIUM; HYDROXYPROPYL METHYLCELLULOSE; TITANIUM DIOXIDE

Prev-Rx

STATEMENT OF IDENTITY

Prev-Rx is indicated for dietary management of patients with unique nutritional needs requiring increased folate, phosphatidyl choline, Vitamin D3, Vitamin B12 or Vitamin E levels or used in improving the nutritional status of patients with folic acid, phosphatidyl choline, Vitamin D3, Vitamin B12 or Vitamin E deficiency. May also be recommended for patients who are advancing in age and may benefit from supplementation to aid in mental acuity. This statement has not been evaluated by the FDA. This product is not intended to diagnose, treat, cure or prevent disease.

DOSAGE AND ADMINISTRATION

Prev-Rx Tablets is an orally administered prescription strength folate product as a dietary supplement.
Prev-Rx should be administered under the supervision of a licensed medical practitioner.

Usual adult dose is 1 tablet daily or as prescribed by a licensed medical practitioner.

HEALTH CLAIM

This product is contraindicated in patients with a known hypersensitivity

WARNINGS

KEEP OUT OF THE REACH OF CHILDREN. In case of accidental overdose, call a doctor or a poison control center immediately. Safety
and effectiveness in pediatric patients has not been established. Tell your doctor if you have: kidney problems, thyroid disease or heart disease.
This medication should only be used as directed by your doctor during pregnancy or while breastfeeding. Consult your doctor about the risk and benefits. Folic acid in doses above 0.1mg daily may obscure pernicious anemia in that hematologic remission can occur while neurological
manifestations progress. There is evidence that the anticonvulsant action of phenytoin is antagonized by folic acid. Patients with epilepsy controlled by phenytoin may require increased dosing of phenytoin.

PRECAUTIONS

Allergic sensitization has been reported following oral administration of folic acid.

SAFE HANDLING WARNING

Store at 20°-25°C (66° to 77°F); excursions permitted to 15°-30°C (59°-86°F) [See USP Controlled Room Temperature]. Protect from
heat, light and moisture.